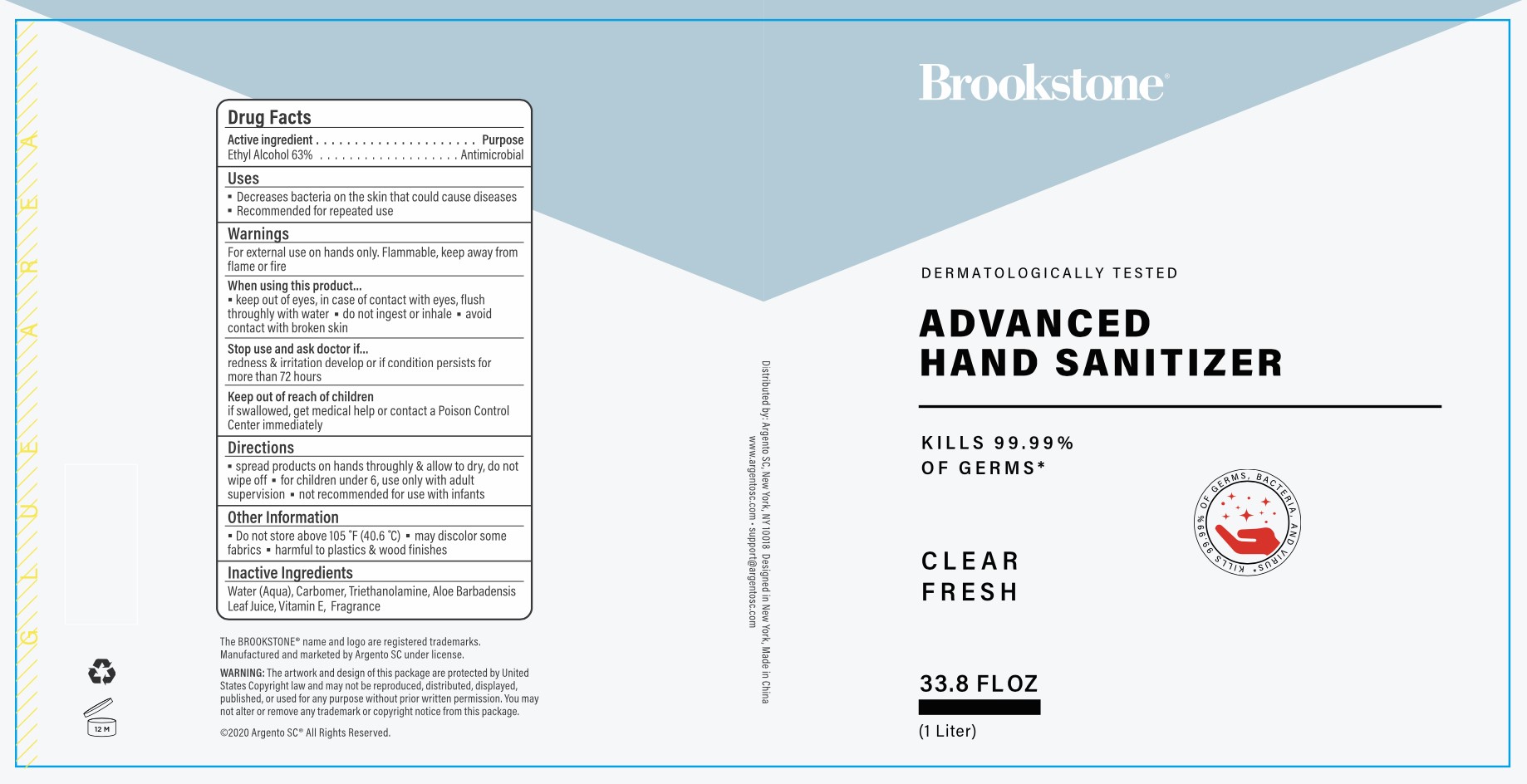 DRUG LABEL: Brookstone Advanced Hand Sanitizer Clear Fresh
NDC: 77731-005 | Form: GEL
Manufacturer: Argento sc by sicura inc.
Category: otc | Type: HUMAN OTC DRUG LABEL
Date: 20200617

ACTIVE INGREDIENTS: ALCOHOL 63 mL/100 mL
INACTIVE INGREDIENTS: CARBOMER 940; TROLAMINE; WATER; ALOE VERA LEAF; .ALPHA.-TOCOPHEROL ACETATE

Active Ingredient(s)

Ethyl Alcohol 63% v/v

Purpose:

Antimicrobial

USE

Decrease bacteria on skin that could cause disease

Recommended for repeated use

warnings

For external use only. Flammable, keep way from flame or fire

When using this product, keep out of eyes. In case of contact with eyes, flush thoroughly with water

Do not ingest or inhale

Avoid contact with broken skin

stop use and ask a doctor

if irrigation and redness develop and condition persists for more than 72 hours

keep out of reach of children

if swallowed,get medical help or contact a Poison Control Center immediately

Directions

- Spread product on hands thoroughly and allow to dry, do not wipe off
- For children under 6, use under adult supervision
- Not recommended for use with infants

other information

Do not store above 105F (40.6C)

May discolor some fabrics

Harmful to plastics and wood finishes

inactive ingredients

Purified water, Carbomer, Triethanolamine, Aloe Barbadensis Leaf Juice, Vitamin E, Fragrance